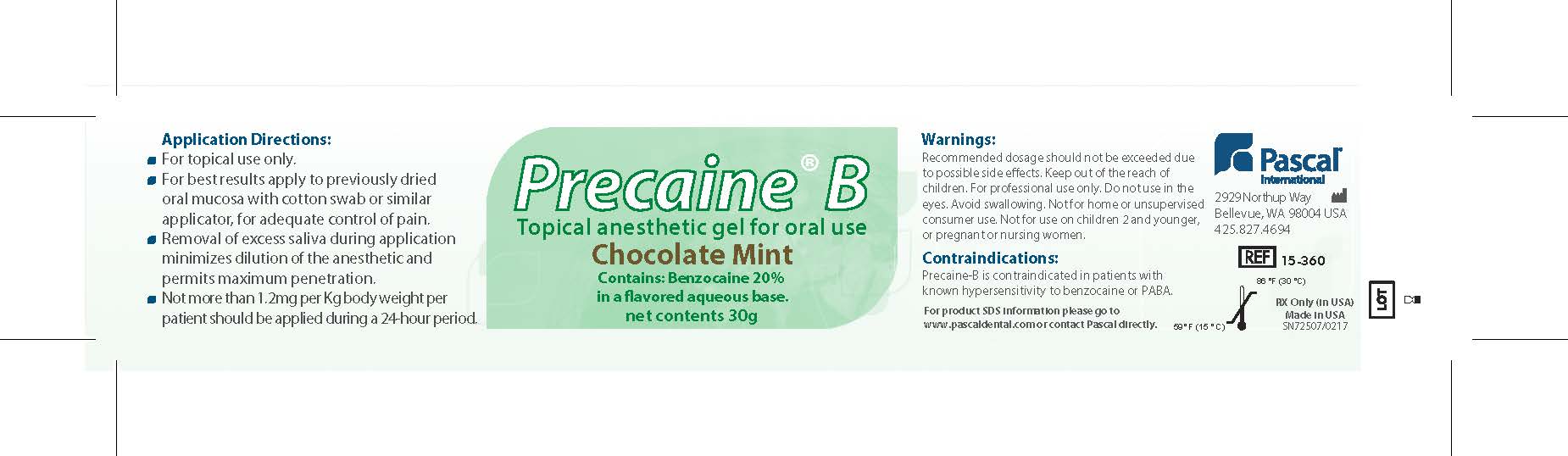 DRUG LABEL: Precaine B Chocolate Mint
NDC: 10866-0090 | Form: GEL
Manufacturer: Pascal Company, Inc.
Category: prescription | Type: HUMAN PRESCRIPTION DRUG LABEL
Date: 20200122

ACTIVE INGREDIENTS: BENZOCAINE 221 mg/1 g

Precaine B Chocolate Mint

Directions:

Application Directions:

For topical use only

For best results apply to previously dried oral mucosa with cotton swab or similar applicator for adequate control of pain

Removal of excess saliva during application minimizes dilution of the anesthetic and permits maximum penetration

Not more than 1.2 mg per Kg body weight per patient should be applied during a 24 hour period

Warnings

Warning:

Recommended dosage should not be exceeded due to possible side effects.

Keep out of the reach of children.

For professional use only.

Do not use in the eye.

Avoid swallowing.

Not for home or unsupervised consumer use.

Not for use on children 2 and younger or pregnant or nursing women.

Contraindications

Precaine B is contraindicated in patients with known hypersensitivity to benzocaine or PABA

Other Information:

For product SDS information, please go to www.pascaldental.com or contact Pascal directly.

Store product between 60 degrees F (16 degrees C) and 86 degrees F (30 degrees C).

Rx only is USA

Made in USA

Precaine B

Topical Anesthetic Gel for Oral Use

Chocolate Mint

Contains: Benzocaine 20% in a flavored aqueous base

Net Contents: 30g

Pascal International

2929 Northup Way

Bellevue, WA 98004

425-827-4694

REF 15-350

SN72507/0217